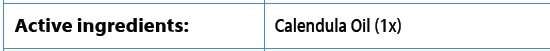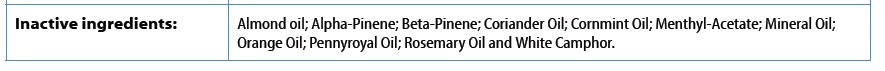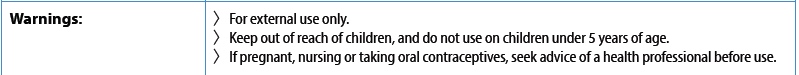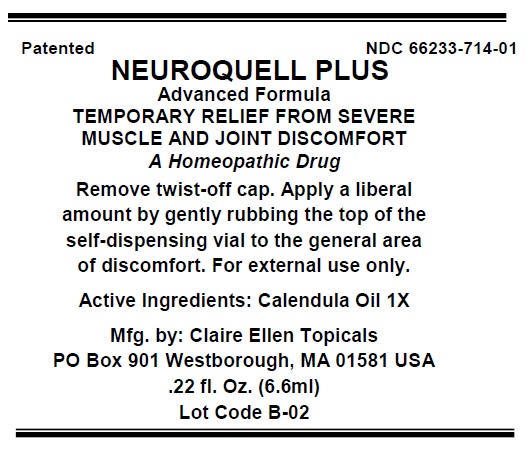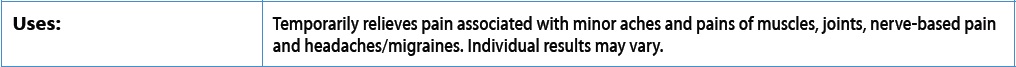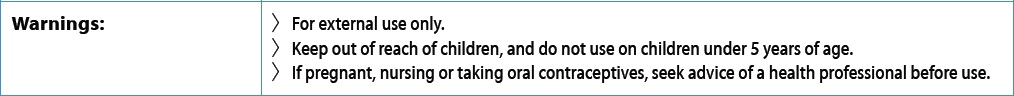 DRUG LABEL: Neuroquell-Plus
NDC: 66233-714 | Form: OIL
Manufacturer: Atlantic Management Resources Inc
Category: homeopathic | Type: HUMAN OTC DRUG LABEL
Date: 20220711

ACTIVE INGREDIENTS: CALENDULA OFFICINALIS FLOWERING TOP 0.015 g/1 g
INACTIVE INGREDIENTS: MINERAL OIL 0.001 g/1 g; ALMOND OIL 0.005 g/1 g; MENTHA ARVENSIS LEAF OIL 0.82 g/1 g; ORANGE OIL 0.007 g/1 g; CAMPHOR OIL, WHITE 0.05 g/1 g; CORIANDER OIL 0.002 g/1 g; PENNYROYAL OIL 0.04 g/1 g; ROSEMARY OIL 0.06 g/1 g

Neuroquell-Plus

DOSAGE & ADMINISTRATION SECTION

When you are ready to apply Neuroquell, remove the cap, turn the bottle upside down, and gently roll the applicator onto the area of discomfort in a continuous, back-and-forth motion to cover approximately one-half of the area of your pain. If using either the sample swab or towelette, apply in a similar way. Your skin will remain moist for a few minutes. Close cap tightly after use, and wash hands thoroughly. Feel free to reapply 4-to-6 hours later and up to 3 additional times per day. To eliminate the peppermint scent, you can wash the treated area with soap and water 15 minutes after the application. This will not affect the efficacy of the product. If there is highlights text then the SPL document title should include the following text string without quotation marks: These highlights do not include all the information needed to use see full prescribing information for and Initial U.S. Approval

INDICATIONS & USAGE SECTION

Temporarily relieves pain associated with minor aches and pains of muscles, joints, nerve-based pain and headaches/migraines. Individual results may vary.